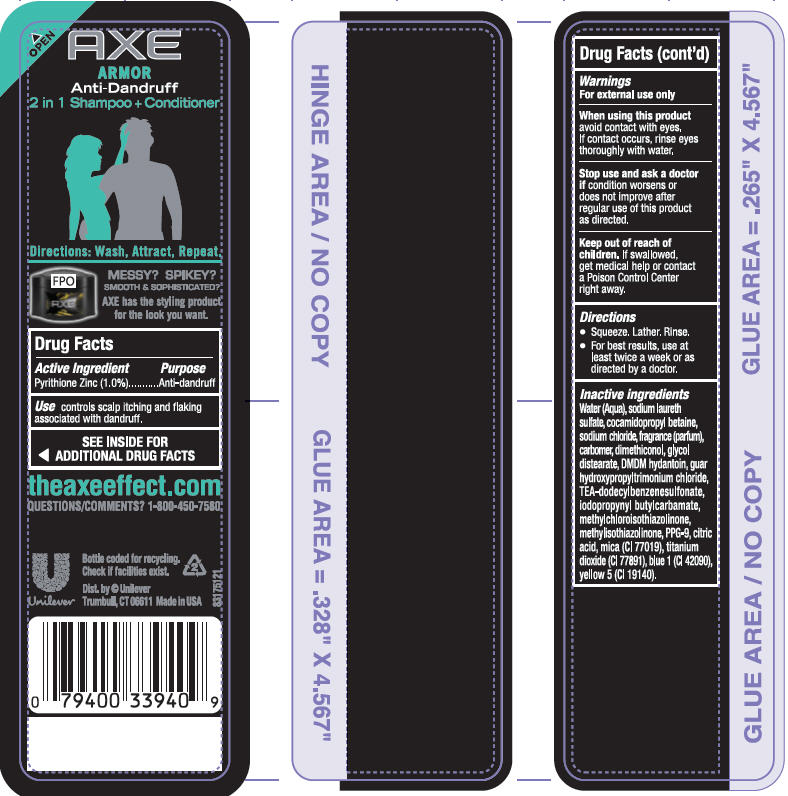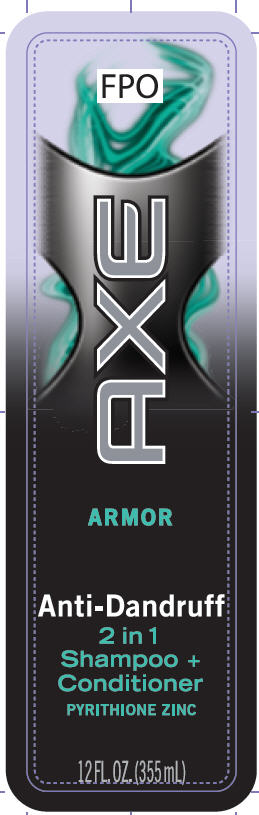 DRUG LABEL: Axe
NDC: 64942-1186 | Form: SHAMPOO
Manufacturer: Conopco Inc. d/b/a Unilever
Category: otc | Type: HUMAN OTC DRUG LABEL
Date: 20110607

ACTIVE INGREDIENTS: Pyrithione Zinc 1 mL/100 mL
INACTIVE INGREDIENTS: WATER; SODIUM LAURETH SULFATE; COCAMIDOPROPYL BETAINE; SODIUM CHLORIDE; CARBOMER HOMOPOLYMER TYPE C; GLYCOL STEARATE; FD&C YELLOW NO. 5; DMDM HYDANTOIN; GUAR HYDROXYPROPYLTRIMONIUM CHLORIDE (1.7 SUBSTITUENTS PER SACCHARIDE); TEA-DODECYLBENZENESULFONATE; CITRIC ACID MONOHYDRATE; IODOPROPYNYL BUTYLCARBAMATE; METHYLCHLOROISOTHIAZOLINONE; METHYLISOTHIAZOLINONE; PPG-9; MICA; TITANIUM DIOXIDE; FD&C BLUE NO. 1

Axe Armor Anti-Dandruff Shampoo

Active Ingredient
Pyrithione Zinc (1.0%)

Purpose
Anti-dandruff

Use
controls scalp itching and flaking associated with dandruff

Warnings
For external use only

When using this product avoid contact with eyes. If contact occurs, rinse eyes thoroughly with water.

Stop use and ask a doctor if condition worsens or does not improve after regular use of this product as directed.

Keep out of reach of children. If swallowed, get medical help or contact a Poison Control Center right away.

Directions
· Squeeze. Lather. Rinse
· For best results, use at least twice a week or as directed by a doctor.

Inactive ingredients
Water (Aqua), Sodium Laureth Sulfate, Cocamidopropyl Betaine, Sodium Chloride, Fragrance (Parfum), Carbomer, Dimethiconol, Glycol Distearate, DMDM Hydantoin, Guar Hydroxypropyltrimonium Chloride, TEA-Dodecylbenzenesulfonate, Citric Acid, Iodopropynyl Butylcarbamate, Methylchloroisothiazolinone, Methylisothiazolinone, PPG-9, Mica (CI 77019), Titanium Dioxide (CI 77891), Blue 1 (CI 42090), Red 33 (CI 17200)

QUESTIONS

theaxeeffect.com
QUESTIONS/COMMENTS?
1-800-450-7580

PACKAGE LABEL

PDP 12 oz front

PACKAGE LABEL

PDP 12 oz back